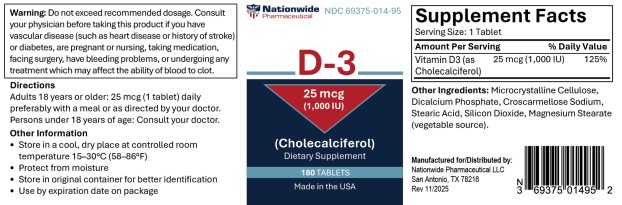 DRUG LABEL: Cholecalciferol 25mcg Tab
NDC: 69375-014 | Form: TABLET
Manufacturer: Nationwide Pharmaceutical LLC
Category: other | Type: DIETARY SUPPLEMENT
Date: 20251205

ACTIVE INGREDIENTS: CHOLECALCIFEROL 25 ug/1 1
INACTIVE INGREDIENTS: MICROCRYSTALLINE CELLULOSE 102; DIBASIC CALCIUM PHOSPHATE DIHYDRATE; STEARIC ACID; CROSCARMELLOSE SODIUM; SILICON DIOXIDE; MAGNESIUM STEARATE

----------
D-3 (Cholecalciferol)

Warning

Do not exceed recommended dosage. Consult your physician before taking this product if you have vascular disease (such as heart disease or history of stroke) or diabetes, are pregnant or nursing, taking medication, facing surgery, have bleeding problems, or undergoing any treatment which may affect the ability of blood to clot.

Directions

Adults 18 years or older: 25 mcg (1 tablet) daily preferably with a meal or as directed by your doctor.

Persons under 18 years of age: Consult your doctor.

Other Information

- Store in a cool, dry place at controlled room temperature 15-30°C (58-86°F)
- Protect from moisture
- Store in original container for better identification
- Use by expiration date on package

Supplement Facts

Serving Size: 1 Tablet

Amount Per Tablet

% Daily Value

Vitamin D3 (as Cholecalciferol)

25 mcg (1,000 IU)

125%

Other Ingredients: Microcrystalline Cellulose, Dicalcium Phosphate, Croscarmellose Sodium, Stearic Acid, Silicon Dioxide, Magnesium Stearate (vegetable source)

Manufactured for/Distributed by:
Nationwide Pharmaceutical LLC
San Antonio, TX 78216
Rev 11/2025

PRINCIPAL DISPLAY PANEL - 25 mcg Tablet Bottle Label

Nationwide
Pharmaceutical
NDC 69375-014-95

D-3

25 mcg

(1,000 IU)

(Cholecalciferol)

Dietary Supplement

180 TABLETS

Made in the USA